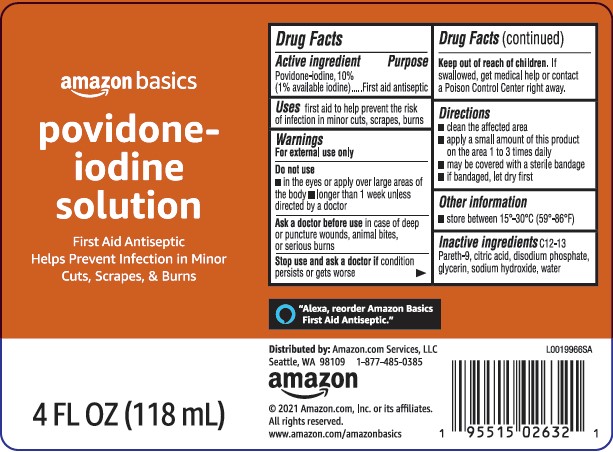 DRUG LABEL: First Aid Antiseptic
NDC: 72288-450 | Form: SOLUTION
Manufacturer: Amazon.Com Services LLC
Category: otc | Type: HUMAN OTC DRUG LABEL
Date: 20250516

ACTIVE INGREDIENTS: POVIDONE-IODINE 10 mg/1 mL
INACTIVE INGREDIENTS: C12-13 PARETH-9; CITRIC ACID MONOHYDRATE; SODIUM PHOSPHATE, DIBASIC, ANHYDROUS; GLYCERIN; SODIUM HYDROXIDE; WATER

Basics 050.002/050AE
Povidone-Iodine

Active ingredient

Povidone-iodine, 10%
(1% available iodine)

Purpose

First aid antiseptic

Use

first aid to help prevent the risk of infection in minor cuts, scrapes and burns

Warnings

For external use only

Do not use

- in the eyes or apply over large areas of the body
- longer than 1 week unless directed by a doctor

Ask a doctor before use

in case of deep or puncture wounds, animal bites, or serious burns

Stop use and ask a doctor

condition persists or gets worse

Keep out of reach of children

If swallowed, get medical help or contact a Poison Control Center right away.

Directions

- clean the affected area
- apply a small amount of this product on the area 1 to 3 times daily
- may be covered with a sterile bandage
- if bandaged, let dry first

Other information

- store between 15º-30ºC (59º-86ºF)

Inactive ingredients

C12-13 Pareth-9, citric acid, disodium phosphate, glycerin, sodium hydroxide, water

ADVERSE REACTION

"Alexa, reorder Amazon Basics First Aid Antiseptic."

DISTRIBUTED BY: Amazon.com, Services, LLC

Seattle, WA 98109 1-877-485-0385

©2021 Amazon.com, Inc. or its affiliates.

All rights reserved.

www.amazon.com/amazonbasics

principal display panel

amazon basics

povidone-

iodine

solution

First Aid Antiseptic

Helps Prevent Infection in Minor Cuts, Scrapes, & Burns

4 FL OZ (118 mL)